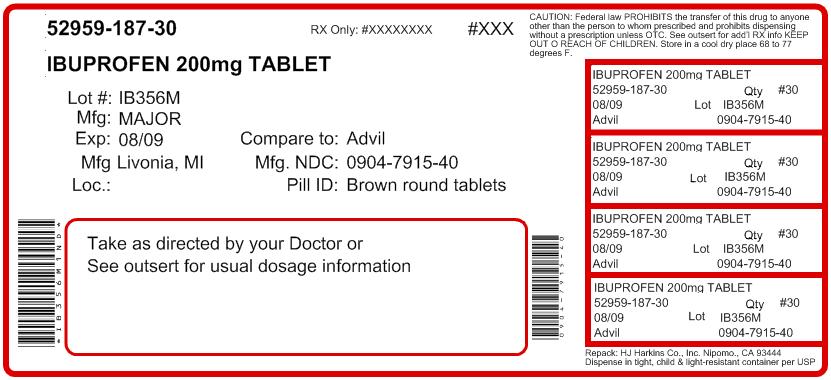 DRUG LABEL: Ibuprofen
NDC: 52959-187 | Form: TABLET, FILM COATED
Manufacturer: H.J. Harkins Company, Inc.
Category: otc | Type: HUMAN OTC DRUG LABEL
Date: 20120208

ACTIVE INGREDIENTS: IBUPROFEN 200 mg/1 1
INACTIVE INGREDIENTS: HYPROMELLOSES; LACTOSE; MAGNESIUM STEARATE; CELLULOSE, MICROCRYSTALLINE; POLYDEXTROSE; POLYETHYLENE GLYCOL; SODIUM STARCH GLYCOLATE TYPE A POTATO; STEARIC ACID

Rite Aid 44-329

Active ingredient(s)

Ibuprofen USP, 200 mg (NSAID)*

*nonsteroidal anti-inflammatory drug

Purpose

Pain reliever/fever reducer

Use(s)

- temporarily relieves minor aches and pains due to:
- headache
- toothache
- backache
- menstrual cramps
- the common cold
- muscular aches
- minor pain of arthritis
- temporarily reduces fever

Warnings

Allergy alert: Ibuprofen may cause a severe allergic reaction, especially in people allergic to aspirin. Symptoms may include:

- hives
- facial swelling
- asthma (wheezing)
- shock
- skin reddening
- rash
- blisters

If an allergic reaction occurs, stop use and seek medical help right away.

Stomach bleeding warning: This product contains an NSAID, which may cause severe stomach bleeding. The chance is higher if you:

- have had stomach ulcers or bleeding problems
- take a blood thinning (anticoagulant) or steroid drug
- take other drugs containing prescription or nonprescription NSAIDs [aspirin, ibuprofen, naproxen, or others]
- have 3 or more alcoholic drinks every day while using this product
- take more or for a longer time than directed

Do not use

- right before or after heart surgery
- if you have ever had an allergic reaction to any other pain reliever/fever reducer

Ask a doctor before use if you have

- stomach bleeding warning applies to you
- you have a history of stomach problems, such as heartburn
- you have high blood pressure, heart disease, liver cirrhosis, or kidney disease
- you are taking a diuretic
- you have asthma
- you have problems or serious side effects from taking pain relievers or fever reducers

Ask a doctor or pharmacist before use if you are

- taking any other drug
- taking aspirin for heart attack or stroke, because ibuprofen may decrease this benefit of aspirin
- under a doctor"s care for any serious condition

When using this product

- take with food or milk if stomach upset occurs
- the risk of heart attack or stroke may increase if you use more than directed or for longer than directed

Stop use and ask a doctor if

- you experience any of the following signs of stomach bleeding:
- feel faint
- have bloody or black stools
- vomit blood
- have stomach pain that does not get better
- pain gets worse or lasts more than 10 days
- fever gets worse or lasts more than 3 days
- redness or swelling is present in the painful area
- any new symptoms appear

If pregnant or breast-feeding,

ask a health professional before use. It is especially important not to use ibuprofen during the last 3 months of pregnancy unless definitely directed to do so by a doctor because it may cause problems in the unborn child or complications during delivery.

Keep out of reach of children

In case of overdose, get medical help or contact a Poison Control Center right away.

Directions

- do not take more than directed
- the smallest effective dose should be used
- do not take longer than 10 days, unless directed by a doctor (see Warnings)
- adults and children 12 years and over: take 1 tablet every 4 to 6 hours while symptoms persist
- if pain or fever does not respond to 1 tablet, 2 tablets may be used
- do not exceed 6 tablets in 24 hours,
- children under 12 years: ask a doctor

Other information

- store between 20°-25°C (68°-77°F)
- avoid excessive heat 40°C (104°F)
- use by expiration date on package

Inactive ingredients

carnauba wax, corn starch, fumed silica gel, hypromellose, lactose, magnesium stearate, microcrystalline cellulose, polydextrose, polyethylene glycol, red iron oxide, sodium starch glycolate, stearic acid, titanium dioxide

Questions?

To Report Adverse Drug Event Call: (800) 616-2471

Principal Display Panel

The product packaging shown below represents a sample of that currently in use. Additional packaging may also be available.

MAJOR®

NDC 0904-7915-80

†Compare to the active ingredient in Advil® Tablets

See New Warnings Information

Ibuprofen

Tablets

Ibuprofen Tablets, USP 200 mg

Pain Reliever

Fever Reducer (NSAID)

1000 COATED TABLETS

TAMPER EVIDENT: DO NOT USE IF IMPRINTED SAFETY SEAD UNDER CAP IS BROKEN OR MISSING

50844 REV0910B29116

Distributed by

MAJOR PHARMACEUTICALS

31778 Enterprise Drive

Livonia, MI 48150 USA M-17 Rev.11/10

Re-order No. 700643

Repacked by:
H.J. Harkins Company, Inc.
Nipomo, CA 93444
Product Packaging